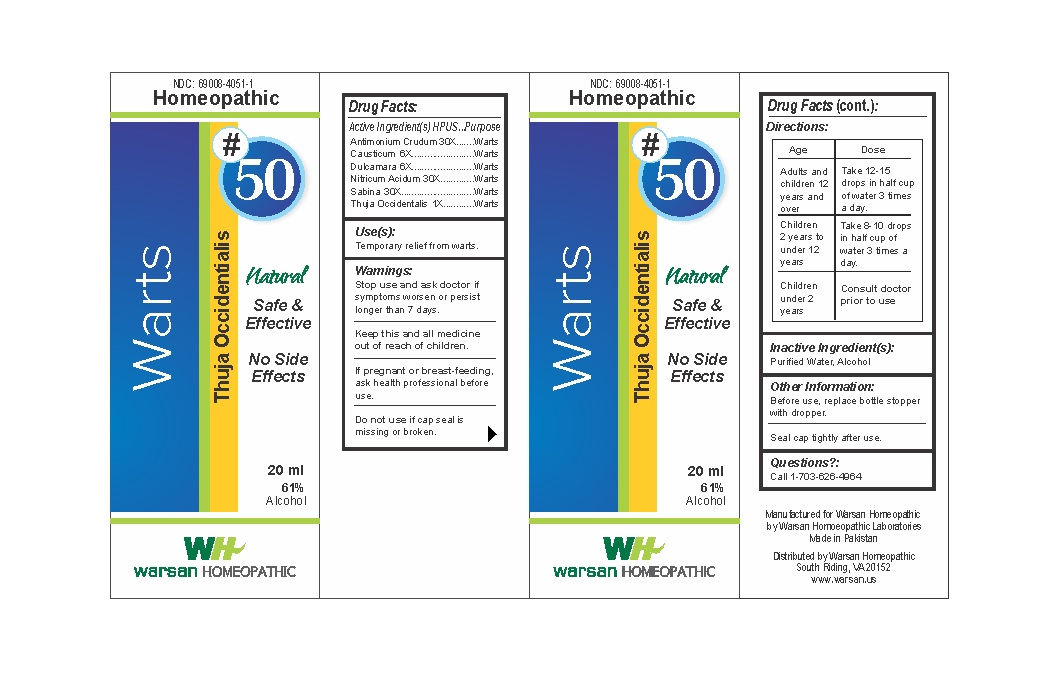 DRUG LABEL: Combination Remedy 50 - Warts
NDC: 69008-4051 | Form: SOLUTION/ DROPS
Manufacturer: Warsan Homoeopathic Laboratories
Category: homeopathic | Type: HUMAN OTC DRUG LABEL
Date: 20171225

ACTIVE INGREDIENTS: SOLANUM DULCAMARA TOP 6 [hp_X]/1 mL; NITRIC ACID 30 [hp_X]/1 mL; ANTIMONY TRISULFIDE 30 [hp_X]/1 mL; THUJA OCCIDENTALIS LEAFY TWIG 1 [hp_X]/1 mL; CAUSTICUM 6 [hp_X]/1 mL; JUNIPERUS SABINA LEAF 30 [hp_X]/1 mL
INACTIVE INGREDIENTS: ALCOHOL; WATER

Stop use and ask doctor if symptoms worsen or persist longer than 7 days.

If pregnant or breast-feeding, ask health professional before use.

Do not use if tamper evident seal is missing or broken.

Keep out of reach of children.

ACTIVE INGREDIENT

Antimonium Crudum 30X

Causticum 6X

Dulcamara 6X

Nitricum Acidum 30X

Sabina 30X

Thuja Occidentalis 1X

PURPOSE

Temporary relief from warts.

INACTIVE INGREDIENT

Purified Water

Alcohol

DOSAGE AND ADMINISTRATION

Adults and children 12 years and older: Take 10-15 drops in half cup of water 3 times a day.

Children 2 years to under 12 years: Take 8-10 drops in half cup of water of 3 times a day.

Children under 2 years: Consult doctor prior to use.

INDICATIONS AND USAGE

Temporary relief from warts.